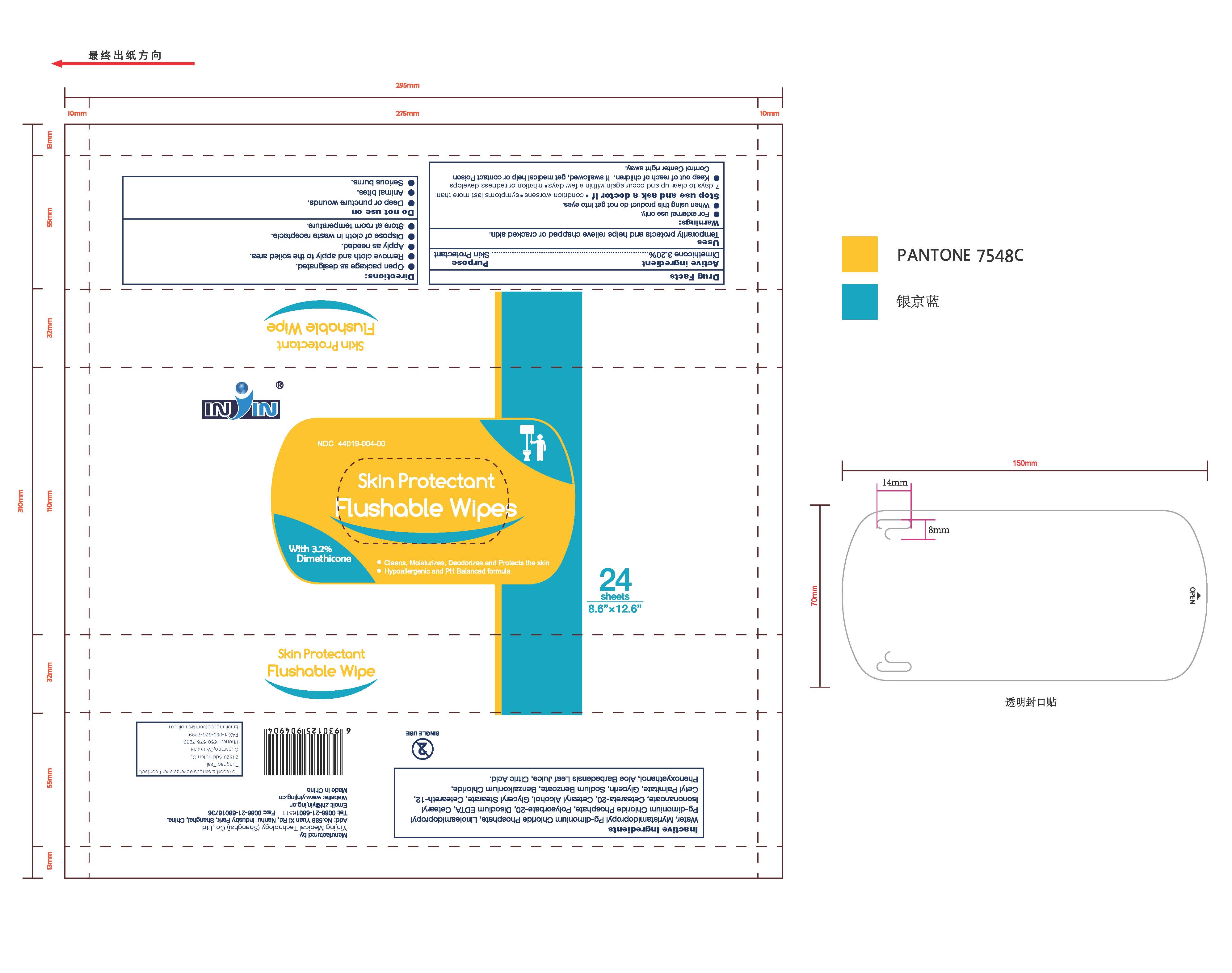 DRUG LABEL: Skin Protectant Flushable Wipes
NDC: 44019-004 | Form: LIQUID
Manufacturer: Yinjing Medical Technology (Shanghai) Co., Ltd.
Category: otc | Type: HUMAN OTC DRUG LABEL
Date: 20171227

ACTIVE INGREDIENTS: DIMETHICONE 3.2 g/100 g
INACTIVE INGREDIENTS: WATER; LINOLEAMIDOPROPYL PG-DIMONIUM CHLORIDE PHOSPHATE; POLYSORBATE 20; EDETATE DISODIUM; CETEARYL ISONONANOATE; POLYOXYL 20 CETOSTEARYL ETHER; CETOSTEARYL ALCOHOL; GLYCERYL MONOSTEARATE; CETEARETH-12; CETYL PALMITATE; GLYCERIN; SODIUM BENZOATE; BENZALKONIUM CHLORIDE; PHENOXYETHANOL; ALOE VERA LEAF; CITRIC ACID MONOHYDRATE

Skin Protectant Flushable Wipes

Active Ingredient

Dimethicone 3.2%

Purpose

Skin Protectant

Use

Temporarily protects and helps relieve chapped or cracked skin

Warnings

For external use only

When using this product do not get into eyes.

Stop use and ask a doctor if

- condition worsens
- symptoms last more than 7 days to clear up and occur again within a few days
- irritation or redness develops

Do not use on

- deep or puncture wounds
- animal bites
- serious burns

Keep out of reach of children. If swallowed, get medical help or contact Poison Control Center right away.

Directions

- Open package as designated
- Remove cloth and apply to the soiled area
- Apply as needed
- Dispose of cloth in waste receptacle or flush in toilet

Other Information

Store at room temperature

Inactive Ingredients

WATER, SODIUM COCO PG-DIMONIUM CHLORIDE PHOSPHATE, LINOLEAMIDOPROPYL PG-DIMONIUM CHLORIDE PHOSPHATE, POLYSORBATE-20, DISODIUM EDTA, CETEARYL ISONONANOATE, CETEARETH-20, CETEARYL ALCOHOL, GLYCERYL STEARATE, CETEARETH-12, CETYL PALMITATE, GLYCERIN, SODIUM BENZOATE, BENZALKONIUM CHLORIDE, PHENOXYETHANOL, ALOE VERA LEAF JUICE, CITRIC ACID